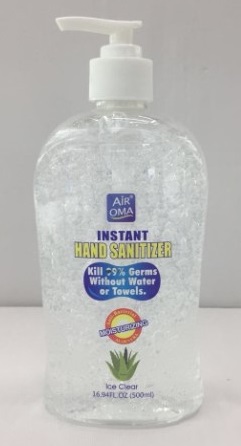 DRUG LABEL: Hand Sanitizer
NDC: 77758-1001 | Form: GEL
Manufacturer: Yiwu Changpeng Daily Commodity Factory
Category: otc | Type: HUMAN OTC DRUG LABEL
Date: 20200513

ACTIVE INGREDIENTS: ALCOHOL 350 mL/500 mL
INACTIVE INGREDIENTS: EDETATE DISODIUM; CARBOMER INTERPOLYMER TYPE A (ALLYL SUCROSE CROSSLINKED); WATER; GLYCERIN; TROLAMINE; CLOVE

Changpeng, Hand Sanitizer, 70% Alcohol, Gel, 500mL

Active Ingredient(s)

Alcohol 70% v/v. Purpose: Antimicrobial

Purpose

Antimicrobial.

Use

Uses for handwashing to decrease bacteria on the skin.

Warnings

For external use only.

Flammable, keep away from heat and flame.

Do not use

Do not us in the eyes. In case of contact, rinse eyes troroughly with water.

When using this product, do not use in or near the eyes or wound.

Stop use and ask a doctor if irritation and redness develop and persist for more than 72 hours.

Keep out of reach of children. If swallowed, get medical help or contact a poison control center right away.

Directions

- Dispense product evenly on palms or on material surface and rub your hands until dry.
- Children should be under adult supervision when using this product.
- No dilute required.

Other information

Store at 20℃ to 25℃.

Inactive ingredients

Carbomer, Glycerin, Triethanolamine, EDTA-2NA, Water, Fragrance